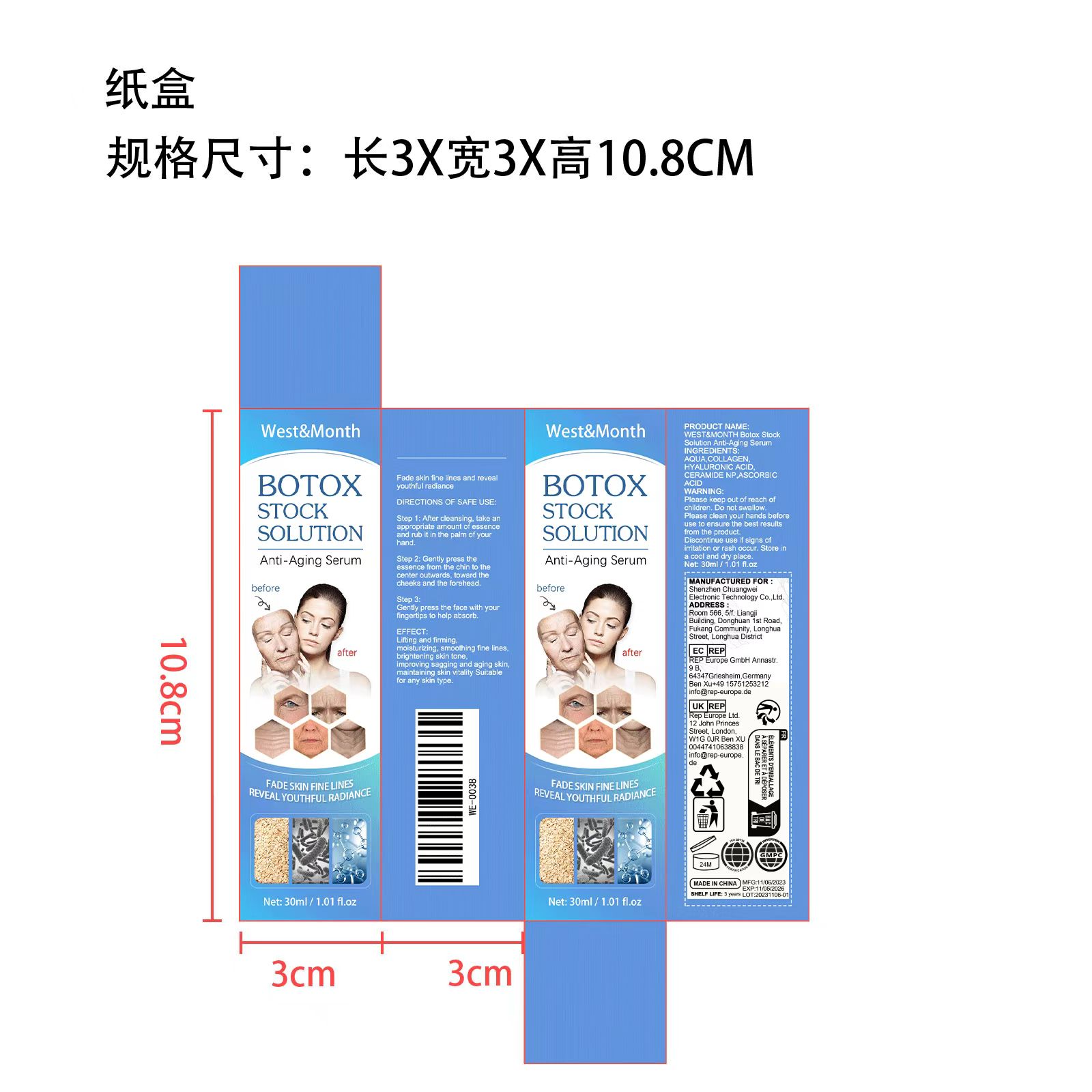 DRUG LABEL: Anti Aging Serum
NDC: 84718-002 | Form: SOLUTION
Manufacturer: Shenzhen Chuangwei Electronic Technology Co., Ltd.
Category: otc | Type: HUMAN OTC DRUG LABEL
Date: 20241022

ACTIVE INGREDIENTS: MARINE COLLAGEN, SOLUBLE 290 g/1000 mL; HYALURONIC ACID 10 g/1000 mL; CERAMIDE NP 20 g/1000 mL; ASCORBIC ACID, (-)- 480 g/1000 mL
INACTIVE INGREDIENTS: WATER

Ingredient

AQUA,COLLAGEN,HYALURONIC ACID.CERAMIDE NP,ASCORBIC ACID

Warnings

Please keep out of reach of children.Do not swallow.Please clean your hands before use to ensure the best results from the product. Discontinue use if signs of irritation or rashoccur. Store in a cool and dry place.

INACTIVE INGREDIENT

none

DOSAGE AND ADMINISTRATION

none

INDICATIONS AND USAGE

none

KEEP OUT OF REACH OF CHILDREN

none